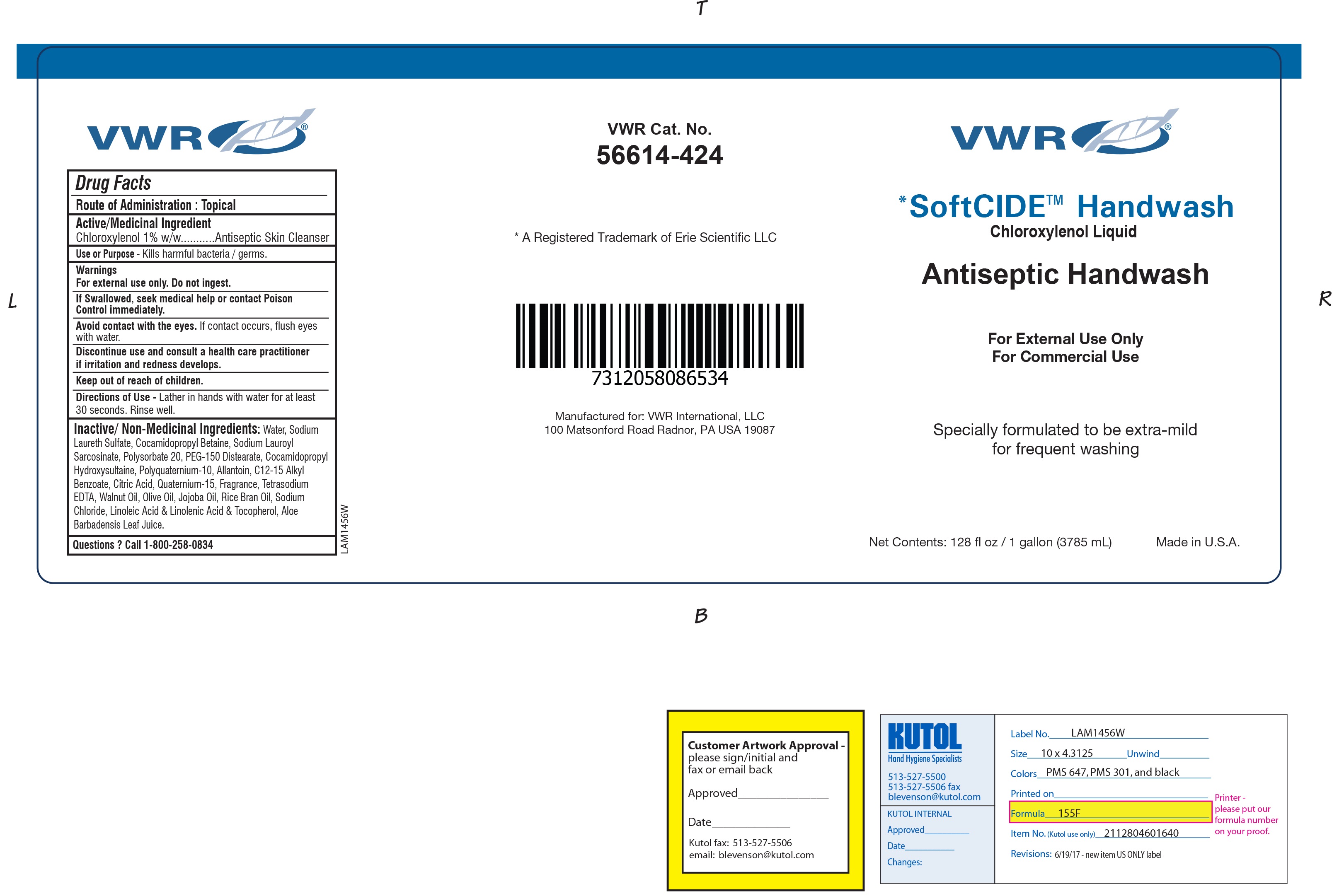 DRUG LABEL: SOFTCIDE
NDC: 71695-200 | Form: SOAP
Manufacturer: VWR International
Category: otc | Type: HUMAN OTC DRUG LABEL
Date: 20230824

ACTIVE INGREDIENTS: CHLOROXYLENOL 0.001 mg/100 mL
INACTIVE INGREDIENTS: PEG-150 DISTEARATE; SODIUM LAUROYL SARCOSINATE; WALNUT OIL; OLIVE OIL; JOJOBA OIL; RICE BRAN OIL; GAMOLENIC ACID; ALKYL (C12-15) BENZOATE; QUATERNIUM-15; EDETATE SODIUM; CITRIC ACID MONOHYDRATE; ALOE VERA LEAF; WATER; POLYQUATERNIUM-10 (30000 MPA.S AT 2%); ALLANTOIN; COCAMIDOPROPYL BETAINE; SODIUM LAURETH SULFATE; COCAMIDOPROPYL HYDROXYSULTAINE; POLYSORBATE 20

VWR F155F

ACTIVE INGREDIENT

CHLOROXYLENOL............1%

PURPOSE

ANTICEPTIVE AGENT

INDICATIONS AND USAGE

Handwash to help reduce bacteria that can potentially cause disease. Reduces the risk and chance of cross -infection.

WARNINGS

For external use only.

If swallowed seek medical help or contact poison control immediately

Avoid contact with eyes. If contact occurs flush with water

Discontinue use and contact a health practitioner if irritation develops

KEEP OUT OF REACH OF CHILDREN

DOSAGE AND ADMINISTRATION

Wet skin and apply a sufficient amount on hands and forearms

Scrub well and rinse thoroughly after washing

INACTIVE INGREDIENT

OLIVE OIL
WALNUT OIL
JOJOBA OIL
RICE BRAN OIL
GAMOLENIC ACID
ALKYL (C12-15) BENZOATE
QUATERNIUM-15
EDETATE SODIUM
CITRIC ACID MONOHYDRATE
ALOE VERA LEAF
POLYQUATERNIUM-10 (30000 MPA.S AT 2%)
ALLANTOIN
COCAMIDOPROPYL BETAINE
SODIUM LAURETH SULFATE
COCAMIDOPROPYL HYDROXYSULTAINE
POLYSORBATE 20
PEG-150 DISTEARATE
SODIUM LAUROYL SARCOSINATE